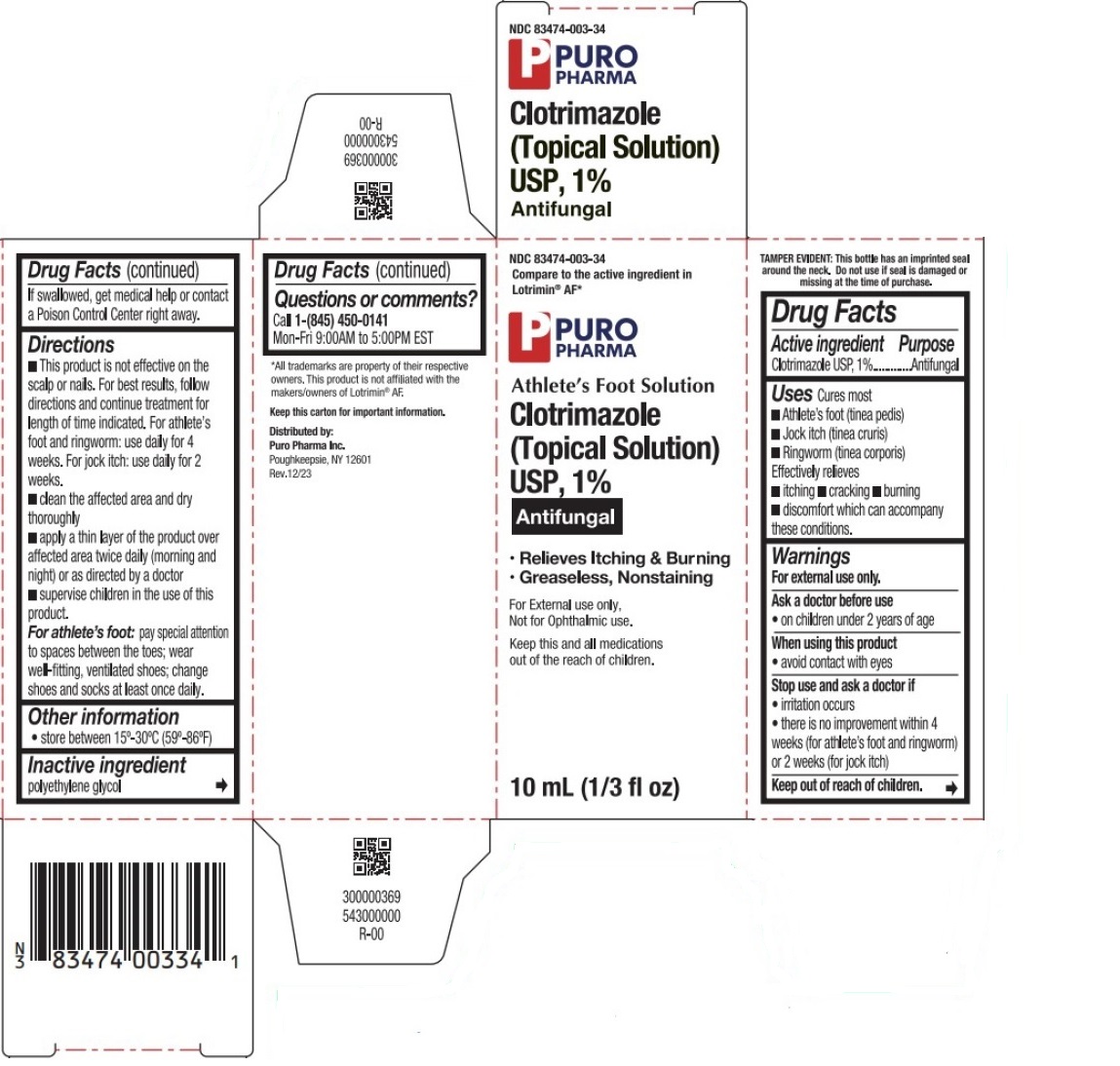 DRUG LABEL: Clotrimazole (Topical Solution), 1%
NDC: 83474-003 | Form: SOLUTION
Manufacturer: Puro Pharma Inc.
Category: otc | Type: HUMAN OTC DRUG LABEL
Date: 20251227

ACTIVE INGREDIENTS: CLOTRIMAZOLE 10 mg/1 mL
INACTIVE INGREDIENTS: POLYETHYLENE GLYCOL, UNSPECIFIED

Clotrimazole (Topical Solution) USP, 1%

Active ingredient

Clotrimazole USP, 1%

Purpose

Antifungal

Uses

Cures most
• Athlete's foot (tinea pedis)
• Jock itch (tinea cruris)
• Ringworm (tinea corporis)

Effectively relieves
• itching • cracking • burning • discomfort which can accompany these conditions.

Warnings

For external use only.

Ask a doctor before use
• on children under 2 years of age

When using this product
• avoid contact with eyes

Stop use and ask a doctor if
• irritation occurs
• there is no improvement within 4 weeks (for athlete's foot and ringworm) or 2 weeks (for jock itch)

Keep out of reach of children.
If swallowed, get medical help or contact a Poison Control Center right away.

Directions

• This product is not effective on the scalp or nails. For best results, follow directions and continue treatment for length of time indicated. For athlete's foot and ringworm: use daily for 4 weeks. For jock itch: use daily for 2 weeks.
• clean the affected area and dry thoroughly
• apply a thin layer of the product over affected area twice daily (morning and night) or as directed by a doctor
• supervise children in the use of this product.
For athlete's foot:pay special attention to spaces between the toes: wear well-fitting, ventilated shoes; change shoes and socks at least once daily.

Other information

• store between 15°-30°C (59°-86°F)

Inactive ingredient

polyethylene glycol

Questions or comments?

Call 1-(845) 450-0141
Mon-Fri 9:00AM to 5:00PM EST

Compare to the active ingredient in Lotrimin® AF*

• Greaseless, Nonstaining

Not for Ophthalmic use.

Keep this and all medications out of the reach of children.

TAMPER EVIDENT: This bottle has an imprinted seal around the neck. Do not use if seal is damaged or missing at the time of purchase.

*All trademarks are property of their respective owners. This product is not affiliated with the makers/owners of Lotrimin®AF.

Keep this carton for important information.

Distributed by:
Puro Pharma Inc.
Poughkeepsie, NY 12601